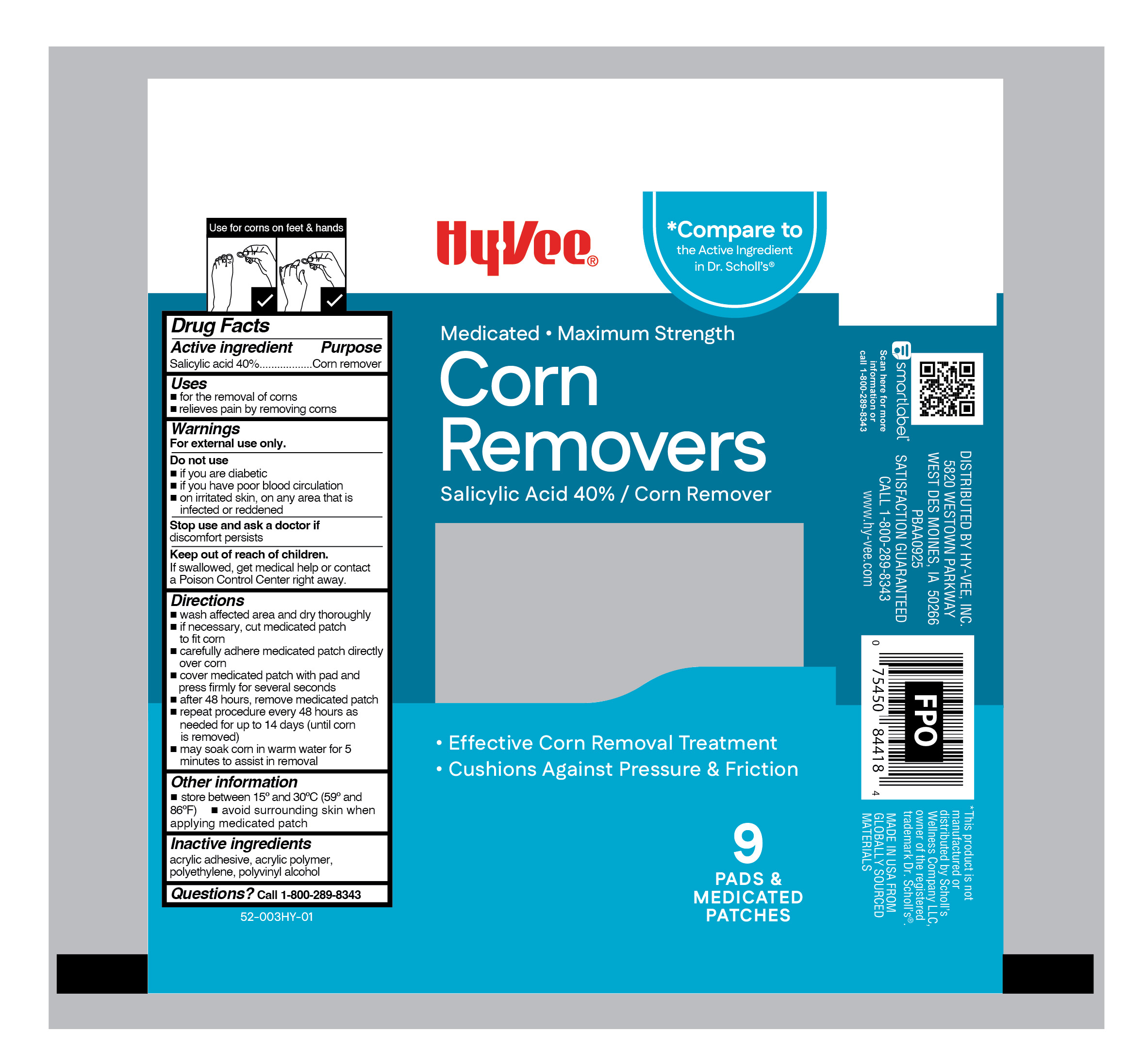 DRUG LABEL: Salicylic Acid
NDC: 42507-999 | Form: PATCH
Manufacturer: HY-VEE, INC
Category: otc | Type: HUMAN OTC DRUG LABEL
Date: 20260102

ACTIVE INGREDIENTS: SALICYLIC ACID 400 mg/1 g
INACTIVE INGREDIENTS: HIGH DENSITY POLYETHYLENE; POLYVINYL ALCOHOL, UNSPECIFIED

Hy-Vee Medicated Corn Removers

Active Ingredient

Salicylic Acid 40%

Purpose

Corn Remover

Uses

- for the removal of corns
- relieves pain by removing corns

Warnings

For External Use Only

Do not use

- if you are diabetic
- if you have poor blood circulation
- on irritated skin, on any area that is infected or reddened

Stop use and ask a doctor if

discomfort persists

Keep out of reach of children.

If swallowed, get medical help or contact a Poison Control Center right away.

Directions

- wash affected area and dry thoroughly
- if necessary, cut medicated patch to fit corn
- carefully adhere medicated patch directly over corn
- cover medicated patch with pad and press firmly for several seconds
- after 48 hours, remove medicated patch
- repeat procedure every 48 hours as needed for up to 14 days (until corn is removed)
- may soak corn in warm water for 5 minutes to assist in removal

Other information

- store between 15° and 30°C (59° and 86°F)
- avoid surrounding skin when applying medicated patch

Inactive ingredients

acrylic adhesive, acrylic polymer, polyethylene, polyvinyl alcohol

Questions?

Call 1-800-289-8343

RECENT MAJOR CHANGES

..

Principal Display Panel

HyVee

Medicated . Maximum Strength

Corn

Removers

Salicylic Acid 40% / Corn Remover

- Effective Corn Removal Treatment
- Cushions Against Pressure & Friction

9

PADS &
MEDICATED

PATCHES